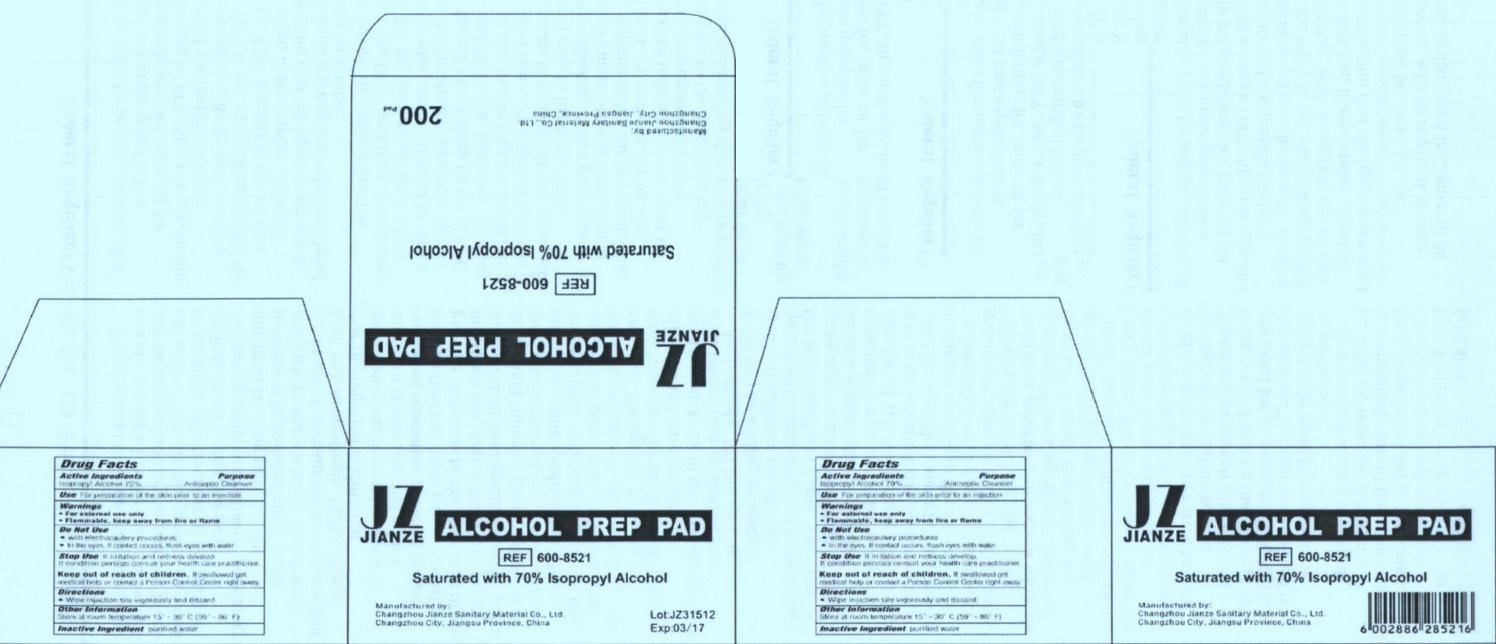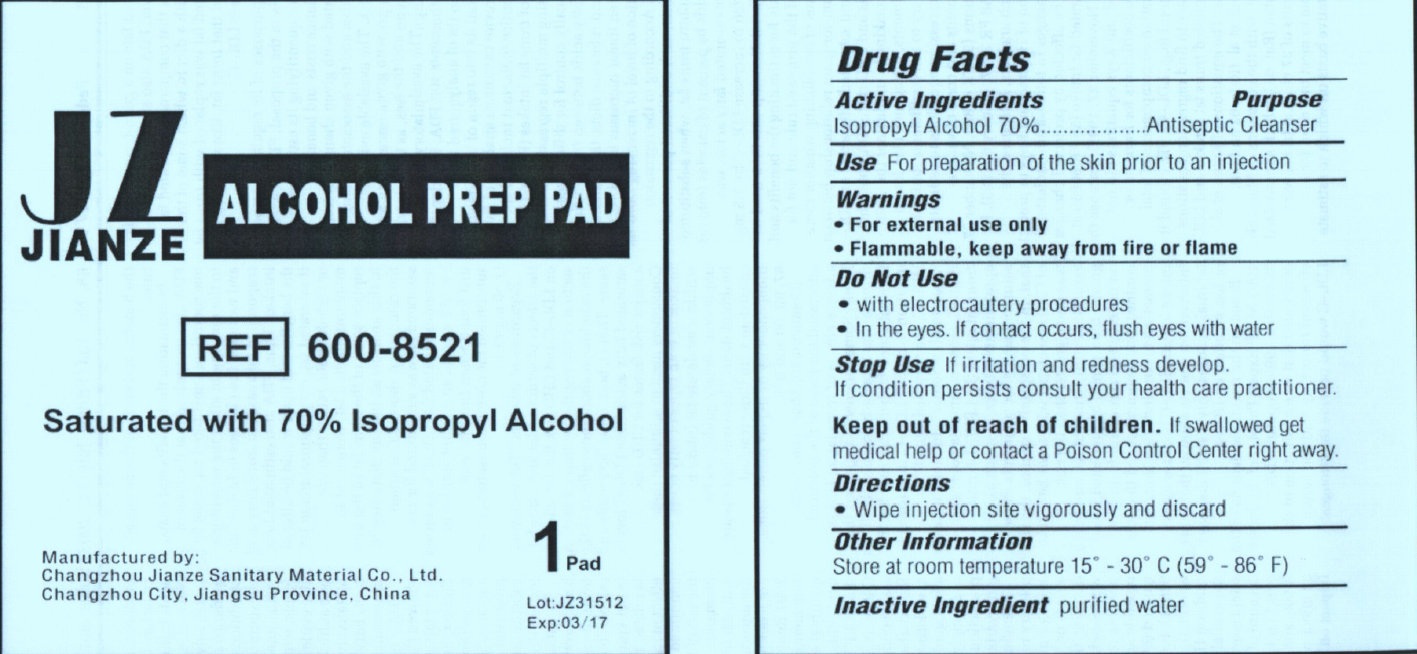 DRUG LABEL: JIANZE ALCOHOL PREP PAD MEDIUM
NDC: 50666-002 | Form: SWAB
Manufacturer: Changzhou Jianze Sanitary Material Co., Ltd.
Category: otc | Type: HUMAN OTC DRUG LABEL
Date: 20120601

ACTIVE INGREDIENTS: ISOPROPYL ALCOHOL 70 mL/100 mL
INACTIVE INGREDIENTS: WATER

JIANZE ALCOHOL PREP PAD MEDIUM

Active Ingredient

Isopropyl Alcohol 70%

Purpose

Antiseptic Cleanser

Use

For preparation of the skin prior to an injection

Warnings

- For external use only
- Flammable, keep away from fire or flame

Do Not Use

- with electrocautery procedures
- In the eyes. If contact occurs, flush with water

Stop Use

If irritation and redness develop.

If condition persists consult your health care practitioner.

Keep out of reach of children

If swallowed get medical help or contact a Poison Control Center right away.

Directions

- Wipe injection site vigorously and discard

Other Information

Store at room temperature 15 degrees - 30 degrees C (59 degrees - 86 degrees F)

Inactive Ingredient

purified water